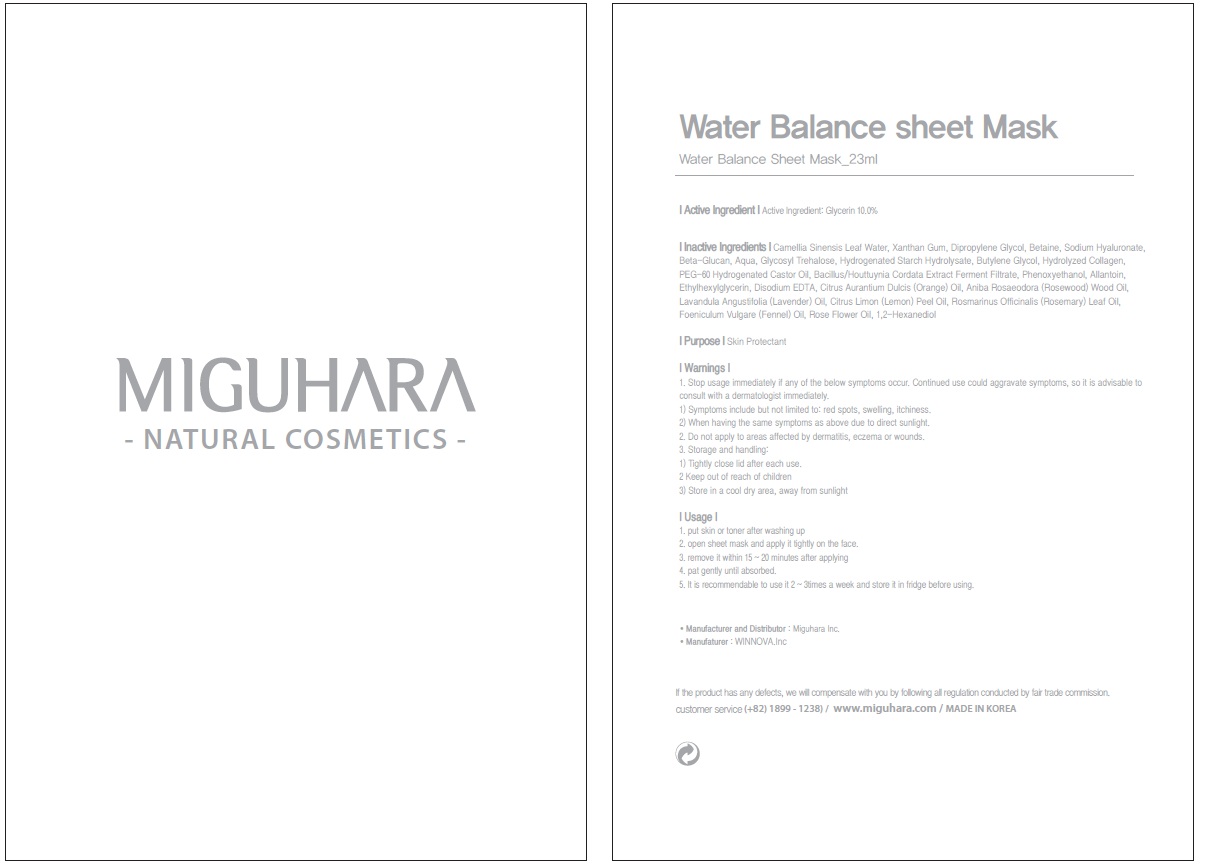 DRUG LABEL: Water Balance Sheet Mask
NDC: 70380-030 | Form: PATCH
Manufacturer: MIGUHARA
Category: otc | Type: HUMAN OTC DRUG LABEL
Date: 20160218

ACTIVE INGREDIENTS: Glycerin 2.3 g/23 mL
INACTIVE INGREDIENTS: GREEN TEA LEAF; Xanthan Gum

ACTIVE INGREDIENT

Active Ingredient: Glycerin 10.0%

INACTIVE INGREDIENT

Inactive Ingredients: Camellia Sinensis Leaf Water, Xanthan Gum, Dipropylene Glycol, Betaine, Sodium Hyaluronate, Beta-Glucan, Aqua, Glycosyl Trehalose, Hydrogenated Starch Hydrolysate, Butylene Glycol, Hydrolyzed Collagen, PEG-60 Hydrogenated Castor Oil, Bacillus/Houttuynia Cordata Extract Ferment Filtrate, Phenoxyethanol, Allantoin, Ethylhexylglycerin, Disodium EDTA, Citrus Aurantium Dulcis (Orange) Oil, Aniba Rosaeodora (Rosewood) Wood Oil, Lavandula Angustifolia (Lavender) Oil, Citrus Limon (Lemon) Peel Oil, Rosmarinus Officinalis (Rosemary) Leaf Oil, Foeniculum Vulgare (Fennel) Oil, Rose Flower Oil, 1,2-Hexanediol

PURPOSE

Purpose: Skin Protectant

WARNINGS

1. Stop usage immediately if any of the below symptoms occur. Continued use could aggravate symptoms, so it is advisable to consult with a dermatologist immediately. 1) Symptoms include but not limited to: red spots, swelling, itchiness. 2) When having the same symptoms as above due to direct sunlight. 2. Do not apply to areas affected by dermatitis, eczema or wounds. 3. Storage and handling: 1) Tightly close lid after each use. 2 Keep out of reach of children 3) Store in a cool dry area, away from sunlight

KEEP OUT OF REACH OF CHILDREN

Usage

1. put skin or toner after washing up 2. open sheet mask and apply it tightly on the face. 3. remove it within 15 ~ 20 minutes after applying 4. pat gently until absorbed. 5. It is recommendable to use it 2 ~ 3times a week and store it in fridge before using.

Usage

1. put skin or toner after washing up 2. open sheet mask and apply it tightly on the face. 3. remove it within 15 ~ 20 minutes after applying 4. pat gently until absorbed. 5. It is recommendable to use it 2 ~ 3times a week and store it in fridge before using.